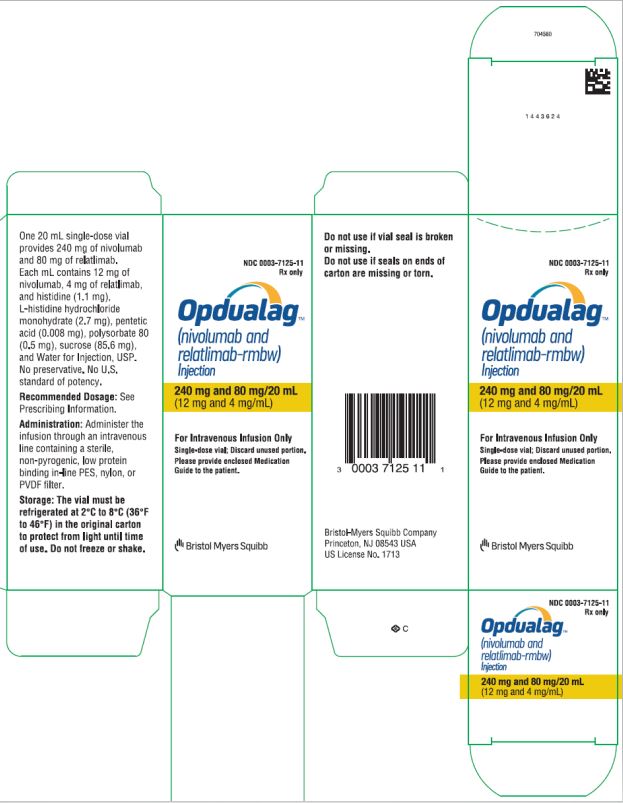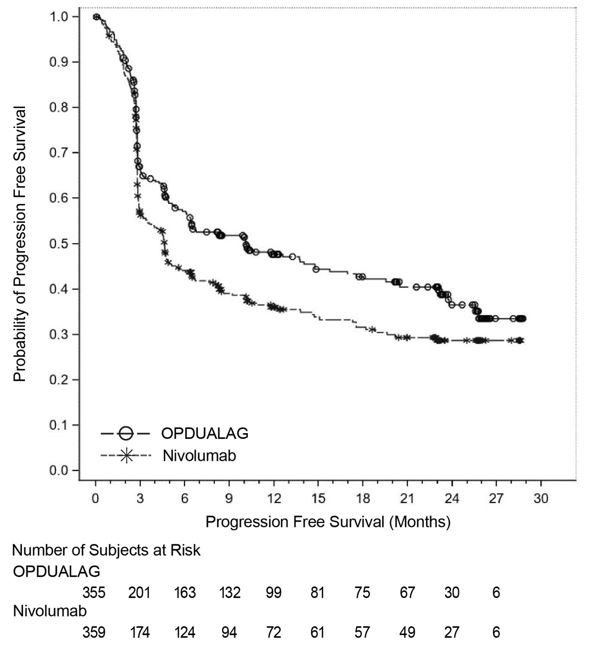 DRUG LABEL: OPDUALAG
NDC: 0003-7125 | Form: INJECTION
Manufacturer: E.R. Squibb & Sons, L.L.C.
Category: prescription | Type: HUMAN PRESCRIPTION DRUG LABEL
Date: 20240301

ACTIVE INGREDIENTS: NIVOLUMAB 12 mg/1 mL; RELATLIMAB 4 mg/1 mL
INACTIVE INGREDIENTS: HISTIDINE 1.1 mg/1 mL; HISTIDINE MONOHYDROCHLORIDE MONOHYDRATE 2.7 mg/1 mL; PENTETIC ACID 0.008 mg/1 mL; POLYSORBATE 80 0.5 mg/1 mL; SUCROSE 85.6 mg/1 mL; WATER

HIGHLIGHTS OF PRESCRIBING INFORMATION

These highlights do not include all the information needed to use OPDUALAG safely and effectively. See full prescribing information for OPDUALAG.
OPDUALAG™ (nivolumab and relatlimab-rmbw) injection, for intravenous use
Initial U.S. Approval: 2022

RECENT MAJOR CHANGES

Warnings and Precautions (5.1) | 3/2024

1 INDICATIONS AND USAGE

OPDUALAG is a combination of nivolumab, a programmed death receptor-1 (PD-1) blocking antibody, and relatlimab, a lymphocyte activation gene-3 (LAG-3) blocking antibody, indicated for the treatment of adult and pediatric patients 12 years of age or older with unresectable or metastatic melanoma. (1)

2 DOSAGE AND ADMINISTRATION

- Adult patients and pediatric patients 12 years of age or older who weigh at least 40 kg: 480 mg nivolumab and 160 mg relatlimab intravenously every 4 weeks. (2)
- Administer OPDUALAG as an intravenous infusion over 30 minutes. (2)
- See full Prescribing Information for dosage modifications for adverse reactions (2.2) and preparation and administration instructions for the injection (2.3).

3 DOSAGE FORMS AND STRENGTHS

- Injection: 240 mg of nivolumab and 80 mg of relatlimab per 20 mL (12 mg and 4 mg per mL) in a single-dose vial. (3)

4 CONTRAINDICATIONS

- None. (4)

5 WARNINGS AND PRECAUTIONS

- Immune-Mediated Adverse Reactions: (5.1)
  - Immune-mediated adverse reactions, which may be severe or fatal, can occur in any organ system or tissue, including the following: immune-mediated pneumonitis, immune-mediated colitis, immune-mediated hepatitis, immune-mediated endocrinopathies, immune-mediated dermatologic adverse reactions, immune-mediated nephritis with renal dysfunction, and immune-mediated myocarditis.
  - Monitor for early identification and management. Evaluate liver enzymes, creatinine, and thyroid function at baseline and periodically during treatment.
  - Withhold or permanently discontinue based on severity and type of reaction. (2.2)
- Infusion-related reactions: Interrupt, slow the rate of infusion, or permanently discontinue OPDUALAG based on severity of reaction. (2.2, 5.2)
- Complications of allogeneic HSCT: Fatal and other serious complications can occur in patient who receive allogeneic HSCT before or after being treated with a PD-1/PD-L1 blocking antibody. (5.3)
- Embryo-fetal toxicity: Can cause fetal harm. Advise females of reproductive potential of potential risk to a fetus and to use effective contraception. (5.4, 8.1, 8.3)

6 ADVERSE REACTIONS

The most common adverse reactions (≥20%) are musculoskeletal pain, fatigue, rash, pruritus, and diarrhea. (6.1)

The most common laboratory abnormalities (≥20%) are decreased hemoglobin, decreased lymphocytes, increased AST, increased ALT, and decreased sodium. (6.1)

To report SUSPECTED ADVERSE REACTIONS, contact Bristol-Myers Squibb at 1-800-721-5072 or FDA at 1-800-FDA-1088 or www.fda.gov/medwatch.

8 USE IN SPECIFIC POPULATIONS

- Lactation: Advise not to breastfeed. (8.2)

FULL PRESCRIBING INFORMATION

1 INDICATIONS AND USAGE

OPDUALAG™ is indicated for the treatment of adult and pediatric patients 12 years of age or older with unresectable or metastatic melanoma.

2 DOSAGE AND ADMINISTRATION

2.1 Recommended Dosage

The recommended dosage of OPDUALAG for adult patients and pediatric patients 12 years of age or older who weigh at least 40 kg is 480 mg nivolumab and 160 mg relatlimab administered intravenously every 4 weeks until disease progression or unacceptable toxicity occurs.

The recommended dosage for pediatric patients 12 years of age or older who weigh less than 40 kg has not been established [see Use in Specific Populations (8.4)].

2.2 Dosage Modifications

No dose reduction for OPDUALAG is recommended. In general, withhold OPDUALAG for severe (Grade 3) immune-mediated adverse reactions (IMARs). Permanently discontinue OPDUALAG for life-threatening (Grade 4) IMARs, recurrent severe (Grade 3) IMARs that require systemic immunosuppressive treatment, or an inability to reduce corticosteroid dose to 10 mg or less of prednisone or equivalent per day within 12 weeks of initiating steroids.

Dosage modifications for adverse reactions that require management different from these general guidelines are summarized in Table 1.

Table 1: Recommended Dosage Modifications for Adverse Reactions
Adverse Reaction | Severity* |  | Dose Modification
Immune-Mediated Adverse Reactions [see Warnings and Precautions (5.1)]
Pneumonitis | Grade 2 |  | Withholda
Pneumonitis | Grade 3 or 4 |  | Permanently discontinue
Colitis | Grade 2 or 3 |  | Withholda
Colitis | Grade 4 |  | Permanently discontinue
Hepatitis | AST/ALT increases to more than 3 and up to 8 times ULN; or; Total bilirubin increases to more than 1.5 and up to 3 times ULN. |  | Withholda
Hepatitis | AST or ALT increases to more than 8 times ULN regardless of baseline.; or; Total bilirubin increases to more than 3 times ULN. |  | Permanently discontinue
Endocrinopathiesb | Grade 3 or 4 |  | Withhold until clinically stable or permanently discontinue depending on severity
Nephritis with Renal Dysfunction | Grade 2 or 3 increased blood creatinine |  | Withholda
Nephritis with Renal Dysfunction | Grade 4 increased blood creatinine |  | Permanently discontinue
Exfoliative Dermatologic Conditions | Suspected SJS, TEN, or DRESS |  | Withhold
Exfoliative Dermatologic Conditions | Confirmed SJS, TEN, or DRESS |  | Permanently discontinue
Myocarditis | Grade 2, 3, or 4 |  | Permanently discontinue
Neurological Toxicities | Grade 2 |  | Withholda
Neurological Toxicities | Grade 3 or 4 |  | Permanently discontinue
Other Adverse Reactions
Infusion-Related Reactions; [see Warnings and Precautions (5.2)] | Grade 1 or 2 |  | Interrupt or slow the rate of infusion
Infusion-Related Reactions; [see Warnings and Precautions (5.2)] | Grade 3 or 4 |  | Permanently discontinue
* Based on National Cancer Institute Common Terminology Criteria for Adverse Events, Version 5.0.
a Resume in patients with complete or partial resolution (Grade 0 to 1) after corticosteroid taper. Permanently discontinue if no complete or partial resolution within 12 weeks of last dose or inability to reduce prednisone to 10 mg per day (or equivalent) or less within 12 weeks of initiating steroids.
b Depending on clinical severity, consider withholding for Grade 2 endocrinopathy until symptom improvement with hormone replacement. Resume once acute symptoms have resolved.
ALT = alanine aminotransferase, AST = aspartate aminotransferase, DRESS = Drug Rash with Eosinophilia and Systemic Symptoms, SJS = Stevens Johnson Syndrome, TEN = toxic epidermal necrolysis, ULN = upper limit normal

2.3 Preparation and Administration

OPDUALAG is a fixed-dose combination of nivolumab and relatlimab.

Visually inspect the solution in the drug product vial for particulate matter and discoloration prior to administration. OPDUALAG is a clear to opalescent, colorless to slightly yellow solution. Discard the vial if the solution is cloudy, discolored, or contains extraneous particulate matter other than a few translucent-to-white particles.

Preparation

- During preparation of the infusion solution, use aseptic technique to assure sterility, as the product does not contain a preservative.
- OPDUALAG can be administered diluted or undiluted and administered at a final concentration as specified in Table 2 below.
- Withdraw the required volume of OPDUALAG and transfer into an intravenous container. OPDUALAG is compatible with di(2-ethylhexyl)phthalate (DEHP)-plasticized polyvinyl chloride (PVC), ethyl vinyl acetate (EVA), and polyolefin (PO) intravenous bags.
- If diluting OPDUALAG prior to administration:
  - Dilute OPDUALAG solution with 0.9% Sodium Chloride Injection, USP or 5% Dextrose Injection, USP to prepare an infusion meeting the final concentration and maximum infusion volume parameters as specified in Table 2 below.
  - Then mix the diluted solution by gentle inversion. Do not shake.
- Discard partially used vials or empty vials following infusion preparation.

Table 2: Maximum Infusion Volumes and Concentration Ranges by Patient Group
Patient Group | Maximum Infusion Volume; (mL or mL/kg) | Concentration Range (mg/mL)*
Adult patients who weigh at least 40 kg and pediatric patients 12 years of age or older who weigh at least 40 kg | 160 mL | Nivolumab: 3 mg/mL to 12 mg/mL; Relatlimab: 1 mg/mL to 4 mg/mL
Adult patients who weigh less than 40 kg | 4 mL/kg | Nivolumab: 3 mg/mL to 12 mg/mL; Relatlimab: 1 mg/mL to 4 mg/mL
* The concentration range in each group includes 12 mg/mL nivolumab and 4 mg/mL relatlimab as the upper limit, which represents a scenario in which the drug product is infused without dilution.

Storage of Prepared Solution

Store the prepared solution either:

- at room temperature and room light for no more than 8 hours from the time of preparation to the end of the infusion. Discard the prepared solution if not used within 8 hours from the time of preparation;

-or-

under refrigeration at 2°C to 8°C (36°F to 46°F) with protection from light for no more than 24 hours from the time of preparation, which includes the time allowed for equilibration of the infusion bag to room temperature and the duration of the infusion. Discard the prepared solution if not used within 24 hours from the time of preparation.

Do not freeze.

Administration

- Administer the infusion over 30 minutes through an intravenous line containing a sterile, non-pyrogenic, low protein binding in-line polyethersulfone (PES), nylon, or polyvinylidene fluoride (PVDF) filter (pore size of 0.2 micrometer to 1.2 micrometer).
- Flush the intravenous line at the end of the infusion.
- Do not coadminister other drugs through the same intravenous line.

3 DOSAGE FORMS AND STRENGTHS

Injection: 240 mg nivolumab and 80 mg relatlimab per 20 mL (12 mg and 4 mg per mL) as a clear to opalescent, colorless to slightly yellow solution in a single-dose vial.

4 CONTRAINDICATIONS

None.

5 WARNINGS AND PRECAUTIONS

5.1 Severe and Fatal Immune-Mediated Adverse Reactions

OPDUALAG potentially breaks peripheral tolerance and induces immune-mediated adverse reactions (IMARs) [see Clinical Pharmacology (12.1)]. Important IMARs listed under Warnings and Precautions may not include all possible severe and fatal IMARs.

IMARs, which may be severe or fatal, can occur in any organ system or tissue. IMARs can occur at any time after starting treatment with a LAG-3 and PD-1/PD-L1 blocking antibodies. While IMARs usually manifest during treatment, IMARs can also manifest after discontinuation.

Early identification and management of IMARs are essential to ensure safe use. Monitor patients closely for symptoms and signs that may be clinical manifestations of underlying IMARs. Evaluate liver enzymes, creatinine, and thyroid function at baseline and periodically during treatment. In cases of suspected IMARs, initiate appropriate workup to exclude alternative etiologies, including infection. Institute medical management promptly, including specialty consultation as appropriate.

Withhold or permanently discontinue OPDUALAG depending on severity [see Dosage and Administration (2.2)]. In general, if OPDUALAG requires interruption or discontinuation, administer systemic corticosteroid therapy (1 to 2 mg/kg/day prednisone or equivalent) until improvement to Grade 1 or less. Upon improvement to Grade 1 or less, initiate corticosteroid taper and continue to taper over at least 1 month. Consider administration of other systemic immunosuppressants in patients whose IMARs are not controlled with corticosteroid therapy.

Toxicity management guidelines for adverse reactions that do not necessarily require systemic steroids (e.g., endocrinopathies and dermatologic reactions) are discussed below.

Immune-Mediated Pneumonitis

OPDUALAG can cause immune-mediated pneumonitis, which may be fatal. In patients treated with other PD-1/PD-L1 blocking antibodies, the incidence of pneumonitis is higher in patients who have received prior thoracic radiation.

Immune-mediated pneumonitis occurred in 3.7% (13/355) of patients receiving OPDUALAG, including Grade 3 (0.6%), and Grade 2 (2.3%) adverse reactions. Pneumonitis led to permanent discontinuation of OPDUALAG in 0.8% and withholding of OPDUALAG in 1.4% of patients.

Systemic corticosteroids were required in 100% (13/13) of patients with pneumonitis. Pneumonitis resolved in 85% of the 13 patients. Of the 5 patients in whom OPDUALAG was withheld for pneumonitis, 5 reinitiated OPDUALAG after symptom improvement; of these, none had recurrence of pneumonitis.

Immune-Mediated Colitis

OPDUALAG can cause immune-mediated colitis, defined as requiring use of corticosteroids and no clear alternate etiology. A common symptom included in the definition of colitis was diarrhea. Cytomegalovirus infection/reactivation has been reported in patients with corticosteroid-refractory immune-mediated colitis. In cases of corticosteroid-refractory colitis, consider repeating infectious workup to exclude alternative etiologies.

Immune-mediated diarrhea or colitis occurred in 7% (24/355) of patients receiving OPDUALAG, including Grade 3 (1.1%) and Grade 2 (4.5%) adverse reactions. Colitis led to permanent discontinuation of OPDUALAG in 2% and withholding of OPDUALAG in 2.8% of patients.

Systemic corticosteroids were required in 100% (24/24) of patients with diarrhea or colitis. Colitis resolved in 83% of the 24 patients. Of the 10 patients in whom OPDUALAG was withheld for colitis, 9 reinitiated OPDUALAG after symptom improvement; of these, 67% had recurrence of colitis.

Immune-Mediated Hepatitis

OPDUALAG can cause immune-mediated hepatitis, defined as requiring the use of corticosteroids and no clear alternate etiology.

Immune-mediated hepatitis occurred in 6% (20/355) of patients receiving OPDUALAG, including Grade 4 (0.6%), Grade 3 (3.4%), and Grade 2 (1.4%) adverse reactions. Hepatitis led to permanent discontinuation of OPDUALAG in 1.7% and withholding of OPDUALAG in 2.3% of patients.

Systemic corticosteroids were required in 100% (20/20) of patients with hepatitis. Hepatitis resolved in 70% of the 20 patients. Of the 8 patients in whom OPDUALAG was withheld for hepatitis, 6 reinitiated OPDUALAG after symptom improvement; of these, 50% had recurrence of hepatitis.

Immune-Mediated Endocrinopathies

Adrenal Insufficiency

OPDUALAG can cause primary or secondary adrenal insufficiency. For Grade 2 or higher adrenal insufficiency, initiate symptomatic treatment, including hormone replacement as clinically indicated. Withhold OPDUALAG depending on severity [see Dosage and Administration (2.2)].

Adrenal insufficiency occurred in 4.2% (15/355) of patients receiving OPDUALAG, including Grade 3 (1.4%) and Grade 2 (2.5%) adverse reactions. Adrenal insufficiency led to permanent discontinuation of OPDUALAG in 1.1% and withholding of OPDUALAG in 0.8% of patients.

Approximately 87% (13/15) of patients with adrenal insufficiency received hormone replacement therapy. Systemic corticosteroids were required in 87% (13/15) of patients with adrenal insufficiency. Adrenal insufficiency resolved in 33% of the 15 patients. Of the 3 patients in whom OPDUALAG was withheld for adrenal insufficiency, all 3 reinitiated OPDUALAG after symptom improvement.

Hypophysitis

OPDUALAG can cause immune-mediated hypophysitis. Hypophysitis can present with acute symptoms associated with mass effect such as headache, photophobia, or visual field defects. Hypophysitis can cause hypopituitarism. Initiate hormone replacement as clinically indicated. Withhold or permanently discontinue OPDUALAG depending on severity [see Dosage and Administration (2.2)].

Hypophysitis occurred in 2.5% (9/355) of patients receiving OPDUALAG, including Grade 3 (0.3%) and Grade 2 (1.4%) adverse reactions. Hypophysitis led to permanent discontinuation of OPDUALAG in 0.3% and withholding of OPDUALAG in 0.6% of patients.

All (9/9) of patients with hypophysitis received hormone replacement therapy. Systemic corticosteroids were required in 100% (9/9) of patients with hypophysitis. Hypophysitis resolved in 22% of the 9 patients. Of the 2 patients in whom OPDUALAG was withheld for hypophysitis, none reinitiated OPDUALAG after symptom improvement.

Thyroid Disorders

OPDUALAG can cause immune-mediated thyroid disorders. Thyroiditis can present with or without endocrinopathy. Hypothyroidism can follow hyperthyroidism. Initiate hormone replacement or medical management as clinically indicated. Withhold or permanently discontinue OPDUALAG depending on severity [see Dosage and Administration (2.2)].

Thyroiditis

Thyroiditis occurred in 2.8% (10/355) of patients receiving OPDUALAG, including Grade 2 (1.1%) adverse reactions. Thyroiditis did not lead to permanent discontinuation of OPDUALAG. Thyroiditis led withholding of OPDUALAG in 0.3% of patients.

Systemic corticosteroids were required in 20% (2/10) of patients with thyroiditis. Thyroiditis resolved in 90% of the 10 patients. For the 1 patient in whom OPDUALAG was withheld for thyroiditis, OPDUALAG was reinitiated after symptom improvement without recurrence of thyroiditis.

Hyperthyroidism

Hyperthyroidism occurred in 6% (22/355) of patients receiving OPDUALAG, including Grade 2 (1.4%) adverse reactions. Hyperthyroidism did not lead to permanent discontinuation of OPDUALAG. Hyperthyroidism led to withholding of OPDUALAG in 0.3% of patients.

Systemic corticosteroids were required in 23% (5/22) of patients. Hyperthyroidism resolved in 82% of the 22 patients. For the 1 patient in whom OPDUALAG was withheld for hyperthyroidism, OPDUALAG was reinitiated after symptom improvement without recurrence of hyperthyroidism.

Hypothyroidism

Hypothyroidism occurred in 17% (59/355) of patients receiving OPDUALAG, including Grade 2 (11%) adverse reactions. Hypothyroidism led to the permanent discontinuation of OPDUALAG in 0.3% and withholding of OPDUALAG in 2.5% of patients.

None of the patients with hypothyroidism required systemic corticosteroids. Hypothyroidism resolved in 12% of the 59 patients. Of the 9 patients in whom OPDUALAG was withheld for hypothyroidism, 6 reinitiated OPDUALAG after symptom improvement; of these, 33% had recurrence of hypothyroidism.

Type 1 Diabetes Mellitus, which can present with Diabetic Ketoacidosis

Monitor patients for hyperglycemia or other signs and symptoms of diabetes. Initiate treatment with insulin as clinically indicated. Withhold or permanently discontinue OPDUALAG depending on severity [see Dosage and Administration (2.2)].

Diabetes occurred in 0.3% (1/355) of patients receiving OPDUALAG, a Grade 3 (0.3%) adverse reaction, and no cases of diabetic ketoacidosis. Diabetes did not lead to the permanent discontinuation or withholding of OPDUALAG in any patient.

Immune-Mediated Nephritis with Renal Dysfunction

OPDUALAG can cause immune-mediated nephritis, which is defined as requiring use of steroids and no clear alternate etiology. Withhold or permanently discontinue OPDUALAG depending on severity [see Dosage and Administration (2.2)].

Immune-mediated nephritis and renal dysfunction occurred in 2% (7/355) of patients receiving OPDUALAG, including Grade 3 (1.1%) and Grade 2 (0.8%) adverse reactions. Immune-mediated nephritis and renal dysfunction led to permanent discontinuation of OPDUALAG in 0.8% and withholding of OPDUALAG in 0.6% of patients.

Systemic corticosteroids were required in 100% (7/7) of patients with nephritis and renal dysfunction. Nephritis and renal dysfunction resolved in 71% of the 7 patients. Of the 2 patients in whom OPDUALAG was withheld for nephritis or renal dysfunction, 1 reinitiated OPDUALAG after symptom improvement without recurrence of nephritis or renal dysfunction.

Immune-Mediated Dermatologic Adverse Reactions

OPDUALAG can cause immune-mediated rash or dermatitis, defined as requiring use of steroids and no clear alternate etiology. Exfoliative dermatitis, including Stevens-Johnson Syndrome, toxic epidermal necrolysis, and Drug Rash with Eosinophilia and Systemic Symptoms has occurred with PD-1/L-1 blocking antibodies. Topical emollients and/or topical corticosteroids may be adequate to treat mild to moderate non-exfoliative rashes. Withhold or permanently discontinue OPDUALAG depending on severity [see Dosage and Administration (2.2)].

Immune-mediated rash occurred in 9% (33/355) of patients receiving OPDUALAG, including Grade 3 (0.6%) and Grade 2 (3.4%) adverse reactions. Immune-mediated rash did not lead to permanent discontinuation of OPDUALAG. Immune-mediated rash led to withholding of OPDUALAG in 1.4% of patients.

Systemic corticosteroids were required in 88% (29/33) of patients with immune-mediated rash. Rash resolved in 70% of the 33 patients. Of the 5 patients in whom OPDUALAG was withheld for immune-mediated rash, 4 reinitiated OPDUALAG after symptom improvement; of these, 25% had recurrence of immune-mediated rash.

Immune-Mediated Myocarditis

OPDUALAG can cause immune-mediated myocarditis, which is defined as requiring use of steroids and no clear alternate etiology. The diagnosis of immune-mediated myocarditis requires a high index of suspicion. Patients with cardiac or cardio-pulmonary symptoms should be assessed for potential myocarditis. If myocarditis is suspected, withhold dose, promptly initiate high dose steroids (prednisone or methylprednisolone 1 to 2 mg/kg/day) and promptly arrange cardiology consultation with diagnostic workup. If clinically confirmed, permanently discontinue OPDUALAG for Grade 2-4 myocarditis [see Dosage and Administration (2.2)].

Myocarditis occurred in 1.7% (6/355) of patients receiving OPDUALAG, including Grade 3 (0.6%), and Grade 2 (1.1%) adverse reactions. Myocarditis led to permanent discontinuation of OPDUALAG in 1.7% of patients.

Systemic corticosteroids were required in 100% (6/6) of patients with myocarditis. Myocarditis resolved in 100% of the 6 patients.

Other Immune-Mediated Adverse Reactions

The following clinically significant IMARs occurred at an incidence of <1% (unless otherwise noted) in patients who received OPDUALAG or were reported with the use of other PD-1/PD-L1 blocking antibodies. Severe or fatal cases have been reported for some of these adverse reactions.

Cardiac/Vascular: Pericarditis, vasculitis.

Nervous System: Meningitis, encephalitis, myelitis and demyelination, myasthenic syndrome/myasthenia gravis (including exacerbation), Guillain-Barré syndrome, nerve paresis, autoimmune neuropathy.

Ocular: Uveitis, iritis, and other ocular inflammatory toxicities can occur. Some cases can be associated with retinal detachment. Various grades of visual impairment, including blindness, can occur. If uveitis occurs in combination with other IMARs, consider a Vogt-Koyanagi-Harada-like syndrome, as this may require treatment with systemic steroids to reduce the risk of permanent vision loss.

Gastrointestinal: Pancreatitis including increases in serum amylase and lipase levels, gastritis, duodenitis.

Musculoskeletal and Connective Tissue: Myositis/polymyositis, rhabdomyolysis (and associated sequelae including renal failure), arthritis, polymyalgia rheumatica.

Endocrine: Hypoparathyroidism.

Other (Hematologic/Immune): Hemolytic anemia, aplastic anemia, hemophagocytic lymphohistiocytosis, systemic inflammatory response syndrome, histiocytic necrotizing lymphadenitis (Kikuchi lymphadenitis), sarcoidosis, immune thrombocytopenic purpura, solid organ transplant rejection, other transplant (including corneal graft) rejection.

5.2 Infusion-Related Reactions

OPDUALAG can cause severe infusion-related reactions. Discontinue OPDUALAG in patients with severe or life-threatening infusion-related reactions. Interrupt or slow the rate of infusion in patients with mild or moderate infusion-related reactions [see Dosage and Administration (2.2)].

In patients who received OPDUALAG as a 60-minute intravenous infusion, infusion-related reactions occurred in 7% (23/355) of patients.

5.3 Complications of Allogeneic Hematopoietic Stem Cell Transplantation

Fatal and other serious complications can occur in patients who receive allogeneic hematopoietic stem cell transplantation (HSCT) before or after being treated with a PD-1/PD-L1 receptor blocking antibody. Transplant-related complications include hyperacute graft-versus-host-disease (GVHD), acute GVHD, chronic GVHD, hepatic veno-occlusive disease after reduced intensity conditioning, and steroid-requiring febrile syndrome (without an identified infectious cause) [see Adverse Reactions (6.1)]. These complications may occur despite intervening therapy between PD-1/PD-L1 blockade and allogeneic HSCT.

Follow patients closely for evidence of transplant-related complications and intervene promptly. Consider the benefit versus risks of treatment with a PD-1/PD-L1 receptor blocking antibody prior to or after an allogeneic HSCT.

5.4 Embryo-Fetal Toxicity

Based on its mechanism of action and data from animal studies, OPDUALAG can cause fetal harm when administered to a pregnant woman. In animal reproduction studies, administration of nivolumab to cynomolgus monkeys from the onset of organogenesis through delivery resulted in increased abortion and premature infant death. Advise pregnant women of the potential risk to a fetus. Advise females of reproductive potential to use effective contraception during treatment with OPDUALAG for at least 5 months after the last dose of OPDUALAG [see Use in Specific Populations (8.1, 8.3)].

6 ADVERSE REACTIONS

The following clinically significant adverse reactions are discussed in greater detail in other sections of the labeling.

- Severe and Fatal IMARs [see Warnings and Precautions (5.1)]
- Infusion-Related Reactions [see Warnings and Precautions (5.2)]
- Complications of Allogeneic HSCT [see Warnings and Precautions (5.3)]

6.1 Clinical Trials Experience

Because clinical trials are conducted under widely varying conditions, adverse reaction rates observed in the clinical trials of a drug cannot be directly compared to rates in the clinical trials of another drug and may not reflect the rates observed in practice.

The safety of OPDUALAG was evaluated in RELATIVITY-047, a randomized (1:1), double-blinded trial in 714 patients with previously untreated metastatic or unresectable melanoma [see Clinical Studies (14)]. Patients received intravenous OPDUALAG (nivolumab 480 mg and relatlimab 160 mg) every 4 weeks (n=355) or nivolumab 480 mg by intravenous infusion every 4 weeks (n=359). Patients were treated with OPDUALAG or nivolumab until disease progression or unacceptable toxicity. The median duration of exposure was 6 months (range: 0 to 31 months) in OPDUALAG-treated patients and 5 months (range: 0 to 32 months) in nivolumab-treated patients.

Serious adverse reactions occurred in 36% of patients treated with OPDUALAG. The most frequent serious adverse reactions reported in ≥1% of patients treated with OPDUALAG were adrenal insufficiency (1.4%), anemia (1.4%), colitis (1.4%), pneumonia (1.4%), acute myocardial infarction (1.1%), back pain (1.1%), diarrhea (1.1%), myocarditis (1.1%), and pneumonitis (1.1%). Fatal adverse reaction occurred in 3 (0.8%) patients who were treated with OPDUALAG; these included hemophagocytic lymphohistiocytosis, acute edema of the lung, and pneumonitis.

OPDUALAG was permanently discontinued due to adverse reactions in 18% of patients. Adverse reactions which resulted in permanent discontinuation of OPDUALAG in ≥1% of patients included myocarditis (1.7%) and pneumonitis (1.4%).

Dosage interruptions due to an adverse reaction occurred in 43% of patients who received OPDUALAG. Adverse reactions that required dosage interruption in ≥2% of patients who received OPDUALAG were diarrhea (3.9%), troponin increased (3.9%), AST increased (2.8%), troponin T increased (2.8%), ALT increased (2.3%), arthralgia (2.3%), hypothyroidism (2.3%), anemia (2%), fatigue (2%), pneumonitis (2%), and rash (2%).

The most common (≥20%) adverse reactions that occurred in patients treated with OPDUALAG were musculoskeletal pain (45%), fatigue (39%), rash (28%), pruritus (25%), and diarrhea (24%). The most common (≥20%) laboratory abnormalities that occurred in patients treated with OPDUALAG were decreased hemoglobin (37%), decreased lymphocytes (32%), increased AST (30%), increased ALT (26%), and decreased sodium (24%).

Tables 3 and 4 summarize both the adverse reactions and laboratory abnormalities, respectively, in RELATIVITY-047.

Table 3: Adverse Reactions in ≥15% of Patients - RELATIVITY-047
Adverse Reaction | OPDUALAG; (n=355) |  | Nivolumab; (n=359)
Adverse Reaction | All Grades (%) | Grades 3-4 (%) | All Grades (%) | Grades 3-4 (%)
Musculoskeletal and Connective Tissue
Musculoskeletal paina | 45 | 4.2 | 31 | 1.7
General
Fatiguea | 39 | 2 | 29 | 0.6
Skin and Subcutaneous Tissue
Rasha | 28 | 1.4 | 21 | 1.9
Pruritus | 25 | 0 | 17 | 0.6
Gastrointestinal
Diarrheaa | 24 | 2 | 17 | 1.4
Nausea | 17 | 0.6 | 14 | 0
Nervous System
Headachea | 18 | 0.3 | 12 | 0.3
Endocrine
Hypothyroidisma | 17 | 0 | 14 | 0
Metabolism and Nutrition Disorders
Decreased appetite | 15 | 0.6 | 7 | 0.3
Respiratory, Thoracic and Mediastinal Disorders
Cougha | 15 | 0.3 | 11 | 0
Toxicity was graded per NCI CTCAE v5.
a Includes multiple terms.

Clinically relevant adverse reactions in <15% of patients who received OPDUALAG included vitiligo, adrenal insufficiency, myocarditis, and hepatitis.

Table 4: Laboratory Abnormalities (≥15%) That Worsened from Baselinea in Patients Who Received OPDUALAG in RELATIVITY-047
Laboratory Abnormality | OPDUALAGa |  | Nivolumaba
Laboratory Abnormality | Grades 1-4 (%) | Grades 3-4 (%) | Grades 1-4 (%) | Grades 3-4 (%)
Chemistry
Increased AST | 30 | 2.3 | 22 | 1.4
Increased ALT | 26 | 3.2 | 25 | 2
Decreased sodium | 24 | 1.2 | 21 | 0.6
Increased alkaline phosphatase | 19 | 0.6 | 17 | 0.9
Increased creatinine | 19 | 0 | 16 | 0
Hematology
Decreased hemoglobin | 37 | 2.7 | 31 | 3.5
Decreased lymphocytes | 32 | 2.5 | 24 | 2.9
a Each test incidence is based on the number of patients who had both baseline and at least one on-study laboratory measurement available: OPDUALAG group (range: 280 to 342 patients) and nivolumab group (range: 276 to 345 patients).

8 USE IN SPECIFIC POPULATIONS

8.1 Pregnancy

Risk Summary

Based on findings in animals and mechanism of action, OPDUALAG can cause fetal harm when administered to a pregnant woman. Administration of nivolumab to cynomolgus monkeys from the onset of organogenesis through delivery resulted in increased abortion and premature infant death (see Data). Human IgG4 is known to cross the placenta; therefore, nivolumab and relatlimab have the potential to be transmitted from the mother to the developing fetus. The effects of OPDUALAG are likely to be greater during the second and third trimesters of pregnancy. There are no available data on OPDUALAG in pregnant women to evaluate a drug-associated risk. Advise the patient of the potential risk to a fetus.

In the U.S. general population, the estimated background risk of major birth defects and miscarriage in clinically recognized pregnancies is 2% to 4% and 15% to 20%, respectively.

Data

Animal Data

OPDUALAG injection for intravenous use contains nivolumab and relatlimab [see Description (11)].

Nivolumab:

One function of the PD-1/PD-L1 pathway is to preserve pregnancy by maintaining immune tolerance to the fetus. The effects of nivolumab on prenatal and postnatal development were evaluated in monkeys that received nivolumab twice weekly from the onset of organogenesis through delivery, at exposure levels of between 9 and 42 times higher than those observed at the clinical dose of 3 mg/kg (based on AUC). Nivolumab administration resulted in a non-dose-related increase in spontaneous abortion and increased neonatal death. In surviving infants (18 of 32 compared to 11 of 16 vehicle-exposed infants) of cynomolgus monkeys treated with nivolumab, there were no apparent malformations and no effects on neurobehavioral, immunological, or clinical pathology parameters throughout the 6-month postnatal period.

Relatlimab:

There are no available animal data on relatlimab. The effects of a murine surrogate anti-LAG-3 antibody was evaluated in mice using syngeneic and allogeneic breeding models. When anti-LAG-3 antibodies were administered beginning on gestation day 6, there were no maternal or developmental effects in either syngeneic or allogeneic breedings.

8.2 Lactation

Risk Summary

There are no data on the presence of nivolumab and relatlimab in human milk, the effects on the breastfed child, or the effects on milk production. Because nivolumab and relatlimab may be excreted in human milk and because of the potential for serious adverse reactions in a breastfed child, advise patients not to breastfeed during treatment with OPDUALAG and for at least 5 months after the last dose [see Pharmacokinetics (12.3)].

8.3 Females and Males of Reproductive Potential

OPDUALAG can cause fetal harm when administered to a pregnant woman [see Use in Specific Populations (8.1)].

Pregnancy Testing

Verify the pregnancy status of females of reproductive potential prior to initiating OPDUALAG [see Use in Specific Populations (8.1)].

Contraception

Advise females of reproductive potential to use effective contraception during treatment and for at least 5 months following the last dose of OPDUALAG [see Clinical Pharmacology (12.3)].

8.4 Pediatric Use

The safety and effectiveness of OPDUALAG for the treatment of unresectable or metastatic melanoma have been established in pediatric patients 12 years of age or older who weigh at least 40 kg. Use of OPDUALAG for this indication is supported by evidence from an adequate and well-controlled study in adults and additional data analyses that suggest that nivolumab and relatlimab exposures in pediatric patients 12 years of age who weigh at least 40 kg are expected to result in similar safety and efficacy to that of adults. The pharmacokinetics of monoclonal antibodies and the course of unresectable or metastatic melanoma are sufficiently similar in adults and pediatric patients 12 years of age or older to allow extrapolation of data from adult patients to pediatric patients 12 years of age or older (who weigh at least 40 kg). A recommended dosage for pediatric patients 12 years of age or older who weigh less than 40 kg has not been established [see Adverse Reactions (6.1), Clinical Pharmacology (12.3), and Clinical Studies (14)].

The safety and effectiveness of OPDUALAG have not been established in pediatric patients 12 years of age or older who weigh less than 40 kg, and pediatric patients younger than 12 years of age.

8.5 Geriatric Use

Of the 355 patients treated with OPDUALAG in RELATIVITY-047, 47% of patients were 65 years or older, 29% were 65 to 74 years, 17% were 75 to 84 years, and 1.7% were 85 years and older. No overall differences in safety or effectiveness were observed between elderly patients and younger patients.

11 DESCRIPTION

Nivolumab and relatlimab-rmbw is a fixed-dose combination of two IgG4 kappa monoclonal antibodies (mAbs). Nivolumab is a programmed death receptor-1 (PD-1) blocking antibody that has a calculated molecular mass of 146 kDa and is expressed in a recombinant Chinese Hamster Ovary (CHO) cell line. Relatlimab is a lymphocyte activation gene-3 (LAG-3) blocking antibody that has a calculated molecular mass of 148 kDa and is expressed in a recombinant CHO cell line.

OPDUALAG (nivolumab and relatlimab-rmbw) injection is a sterile, preservative-free, clear to opalescent, colorless to slightly yellow solution that may contain few translucent-to-white particles. OPDUALAG is supplied as 240 mg of nivolumab and 80 mg of relatlimab in a 20 mL single-dose vial for intravenous use. Each mL of OPDUALAG solution contains 12 mg of nivolumab, 4 mg of relatlimab, and histidine (1.1 mg), L-histidine hydrochloride monohydrate (2.7 mg), pentetic acid (0.008 mg), polysorbate 80 (0.5 mg), sucrose (85.6 mg), and Water for Injection, USP. The pH is 5.8.

12 CLINICAL PHARMACOLOGY

12.1 Mechanism of Action

Relatlimab is a human IgG4 monoclonal antibody that binds to the LAG-3 receptor, blocks interaction with its ligands, including MHC II, and reduces LAG-3 pathway-mediated inhibition of the immune response. Antagonism of this pathway promotes T cell proliferation and cytokine secretion.

Binding of the PD-1 ligands, PD-L1 and PD-L2, to the PD-1 receptor found on T cells, inhibits T-cell proliferation and cytokine production. Upregulation of PD-1 ligands occurs in some tumors, and signaling through this pathway can contribute to inhibition of active T-cell immune surveillance of tumors. Nivolumab is a human IgG4 monoclonal antibody that binds to the PD-1 receptor, blocks interaction with its ligands PD-L1 and PD-L2, and reduces PD-1 pathway-mediated inhibition of the immune response, including the anti-tumor immune response. In syngeneic mouse tumor models, blocking PD-1 activity resulted in decreased tumor growth.

The combination of nivolumab (anti-PD-1) and relatlimab (anti-LAG-3) results in increased T-cell activation compared to the activity of either antibody alone. In murine syngeneic tumor models, LAG-3 blockade potentiates the anti-tumor activity of PD-1 blockage, inhibiting tumor growth and promoting tumor regression.

12.2 Pharmacodynamics

The exposure-response relationship and time course of pharmacodynamic response for the safety and effectiveness of OPDUALAG have not been fully characterized.

12.3 Pharmacokinetics

The pharmacokinetics (PK) of relatlimab following the administration of OPDUALAG were characterized in patients with cancer who received relatlimab 20 to 800 mg every 2 weeks (0.25 to 10 times the approved recommended dosage) or 160 to 1440 mg every 4 weeks (1 to 9 times the approved recommended dosage) either as a monotherapy or in combination with nivolumab dosages of 80 or 240 mg every 2 weeks or 480 mg every 4 weeks.

Steady-state concentrations of relatlimab were reached by 16 weeks with an every 4-week regimen and the systemic accumulation was 1.9-fold. The average concentration (Cavg) of relatlimab after the first dose increased dose proportionally at doses ≥160 mg every 4 weeks.

Following the recommended dosage, the geometric mean [coefficient of variation (CV%)] maximum and average concentrations (Cmax and Cavg) of relatlimab at steady state were 62.2 (30%), and 28.8 (45%) μg/mL, respectively; and the mean Cmax and Cavg of nivolumab at steady state were 187 (33%) and 94.4 (43%) μg/mL, respectively.

In RELATIVITY-047, the nivolumab geometric mean minimum concentration (Cmin) at steady state in the OPDUALAG arm was comparable to the nivolumab arm.

Distribution

The geometric mean (CV%) volume of distribution at steady state of relatlimab is 6.6 L (20%) and 6.6 L (19%) of nivolumab.

Elimination

The geometric mean (CV%) clearance of relatlimab is 5.5 mL/h (41%) at steady state, 10% lower than after the first dose [6 mL/h (39%)]. Following OPDUALAG (nivolumab 480 mg and relatlimab 160 mg administered every 4 weeks) administration, the geometric mean (CV%) effective half-life (t1/2) of relatlimab is 26.2 days (37%).

The geometric mean (CV%) clearance of nivolumab is 7.6 mL/h (40%) at steady state, 21% lower than after the first dose [9.6 mL/h (40%)] and the terminal t1/2 is 26.5 days (36%).

Specific Populations

The following factors had no clinically important effect on the clearance of nivolumab and relatlimab: age (17 to 92 years), sex, race (White, Asian, and Black/African American), mild or moderate renal impairment (eGFR 30 to 89 mL/min/1.73 m^2), mild hepatic impairment (total bilirubin [TB] less than or equal to upper limit of normal [ULN] and AST greater than ULN or TB greater than 1 to 1.5 times ULN and any AST) or moderate hepatic impairment (TB greater than 1.5 to 3 times ULN and any AST). The effects of severe renal impairment, or severe hepatic impairment on the pharmacokinetics of nivolumab and relatlimab are unknown.

Pediatric patients:

The exposures of nivolumab and relatlimab in pediatric patients 12 years of age or older who weigh at least 40 kg are expected to be in the range of exposures in adult patients at the recommended dosage.

12.6 Immunogenicity

The observed incidence of anti-drug antibodies is highly dependent on the sensitivity and specificity of the assay. Differences in assay methods preclude meaningful comparisons of the incidence of anti-drug antibodies in the studies described below with the incidence of anti-drug antibodies in other studies, including studies of nivolumab and relatlimab-rmbw products, or nivolumab products.

During the initial 24-month treatment period in RELATIVITY-047, the incidence of:

- anti-nivolumab antibodies and neutralizing antibodies in the OPDUALAG group was 3.8% (11/288) and 0.3% (1/288), respectively, which was similar to that observed in the nivolumab group: 5.9% (16/272) and 0.4% (1/272), respectively.
- anti-relatlimab antibodies and neutralizing antibodies in the OPDUALAG group was 5.6% (16/286) and 0.3% (1/286), respectively.

Because of the low incidence of anti-drug antibodies, the effect of these antibodies on the pharmacokinetics, pharmacodynamics, safety, or effectiveness of OPDUALAG is unknown.

13 NONCLINICAL TOXICOLOGY

13.1 Carcinogenesis, Mutagenesis, Impairment of Fertility

OPDUALAG contains nivolumab and relatlimab.

No studies have been performed to assess the potential of nivolumab or relatlimab for carcinogenicity or genotoxicity. Fertility studies have not been performed with nivolumab or relatlimab.

13.2 Animal Toxicology and/or Pharmacology

In animal models, inhibition of PD-1 signaling increased the severity of some infections and enhanced inflammatory responses. Mycobacterium tuberculosis–infected PD-1 knockout mice exhibited markedly decreased survival compared with wild-type controls, which correlated with increased bacterial proliferation and inflammatory responses in these animals. PD-1 blockade using a primate anti-PD-1 antibody was also shown to exacerbate M. tuberculosis infection in rhesus macaques. PD-1 and PD-L1 knockout mice receiving PD-L1 blocking antibody have also shown decreased survival following infection with lymphocytic choriomeningitis virus.

Inhibition of PD-1 and LAG-3 results in autoimmunity in preclinical models. Mice deficient in both PD-1 and LAG-3 develop lethal systemic autoimmunity that includes myocarditis.

In a 1-month study in monkeys dosed with nivolumab and relatlimab, inflammation within the central nervous system (choroid plexus, vasculature, meninges, spinal cord) and the reproductive tract (epididymis, seminal vesicles, and testes) was observed.

14 CLINICAL STUDIES

The efficacy of OPDUALAG was investigated in RELATIVITY-047 (NCT03470922), a randomized (1:1), double-blinded trial in 714 patients with previously untreated metastatic or unresectable Stage III or IV melanoma. Patients were allowed to have received prior adjuvant or neoadjuvant melanoma therapy: anti-PD-1, anti-CTLA-4, or BRAF-MEK inhibitors were allowed if received at least 6 months between the last dose of therapy and date of recurrence; interferon therapy was allowed if the last dose was at least 6 weeks prior to randomization. The trial excluded patients with active autoimmune disease, medical conditions requiring systemic treatment with moderate or high dose corticosteroids or immunosuppressive medications, uveal melanoma, and active or untreated brain or leptomeningeal metastases. Patients were randomized to receive OPDUALAG (nivolumab 480 mg and relatlimab 160 mg) by intravenous infusion every 4 weeks (n=355) or nivolumab 480 mg by intravenous infusion every 4 weeks (n=359) until disease progression or unacceptable toxicity. Randomization was stratified by tumor PD-L1 expression (≥1% vs. <1%) using PD-L1 IHC 28-8 pharmDx test, LAG-3 expression (≥1% vs. <1%) using a clinical trial assay, BRAF V600 mutation status (V600 mutation positive vs. wild type), and M stage per the American Joint Committee on Cancer (AJCC) version 8 staging system (M0/M1any[0] vs. M1any[1]).

The major efficacy outcome measure was progression-free survival (PFS) determined by Blinded Independent Central Review (BICR) using Response Evaluation Criteria in Solid Tumors (RECIST v1.1). Additional efficacy outcome measures were overall survival (OS) and overall response rate (ORR) determined by BICR using RECIST v1.1. Tumor assessments were conducted 12 weeks after randomization and continued every 8 weeks up to week 52 and then every 12 weeks.

The trial population characteristics were: median age 63 years (range: 20 to 94); 58% male; 97% White 0.7% African American, and American Indian/Alaskan Native 0.1%; Hispanic 7%; and ECOG performance score was 0 (67%) or 1 (33%). Disease characteristics were: PD-L1 expression ≥1% (41%), LAG-3 expression ≥1% (75%), AJCC Stage IV disease (92%), M1c disease (39%); M1d disease (2.4%), elevated LDH (36%), and BRAF V600 mutation-positive melanoma (39%).

The trial demonstrated a statistically significant improvement in PFS for patients randomized to the OPDUALAG arm compared with the nivolumab arm. The final analysis of OS was not statistically significant. Efficacy results are shown in Table 5 and Figure 1.

Table 5: Efficacy Results in RELATIVITY-047
 | OPDUALAG; N=355 | Nivolumab; N=359
Progression-free Survivala,b
Disease progression or death (%) | 180 (51) | 211 (59)
Median (months)c (95% CI) | 10.1 (6.4, 15.7) | 4.6 (3.4, 5.6)
Hazard ratiod (95% CI) | 0.75 (0.62, 0.92)
p-valuee | 0.0055
Overall Survivalf
Deaths (%) | 137 (39) | 160 (45)
Median in months (95% CI) | NR (34.2, NR) | 34.10 (25.2, NR)
Hazard ratiod (95% CI) | 0.80 (0.64, 1.01)
p-valuee | NSg
Overall Response Ratea,f, h, n (%); (95% CI) | 153 (43); (38, 48) | 117 (33); (28, 38)
Complete response rate (%) | 58 (16) | 51 (14)
Partial response rate (%) | 95 (27) | 66 (18)
a Assessed by BICR.
b Final PFS analysis.
c Kaplan-Meier estimate.
d Based on stratified Cox proportional hazard model.
e Based on stratified log-rank test.
f At the time of the final OS analysis, which was event-driven and occurred after the final PFS analysis.
g Not Significant at alpha level 0.04302.
h Not formally tested based on the testing hierarchy.
NR = Not reached.

Figure 1: Progression-free Survival - RELATIVITY-047

16 HOW SUPPLIED/STORAGE AND HANDLING

OPDUALAG (nivolumab and relatlimab-rmbw) injection is a sterile, preservative-free, clear to opalescent, colorless to slightly yellow solution for intravenous use supplied in a single-dose vial containing 240 mg of nivolumab and 80 mg of relatlimab per 20 mL (12 mg and 4 mg per mL) per carton (NDC 0003-7125-11).

Store OPDUALAG refrigerated at 2°C to 8°C (36°F to 46°F) in the original carton to protect from light until time of use. Do not freeze or shake.

17 PATIENT COUNSELING INFORMATION

Advise the patient to read the FDA-approved patient labeling (Medication Guide).

Immune-Mediated Adverse Reactions (IMAR)

Inform patients of the risk of IMARs that may require corticosteroid treatment and withholding or discontinuation of OPDUALAG, including:

- Pneumonitis: Advise patients to contact their healthcare provider immediately for any new or worsening cough, chest pain, or shortness of breath [see Warnings and Precautions (5.1)].
- Colitis: Advise patients to contact their healthcare provider immediately for diarrhea or severe abdominal pain [see Warnings and Precautions (5.1)].
- Hepatitis: Advise patients to contact their healthcare provider immediately for jaundice, severe nausea or vomiting, pain on the right side of abdomen, lethargy, or easy bruising or bleeding [see Warnings and Precautions (5.1)].
- Endocrinopathies: Advise patients to contact their healthcare provider immediately for signs or symptoms of hypophysitis, adrenal insufficiency, thyroiditis, hypothyroidism, hyperthyroidism, and diabetes mellitus [see Warnings and Precautions (5.1)].
- Nephritis with Renal Dysfunction: Advise patients to contact their healthcare provider immediately for signs or symptoms of nephritis, including decreased urine output, blood in urine, swelling in ankles, loss of appetite, and any other symptoms of renal dysfunction [see Warnings and Precautions (5.1)].
- Skin Adverse Reactions: Advise patients to contact their healthcare provider immediately for rash [see Warnings and Precautions (5.1)].
- Myocarditis: Advise patients to contact their healthcare provider immediately for signs or symptoms of new or worsening chest pain, palpitations, shortness of breath, fatigue, or swelling in ankles [see Warnings and Precautions (5.1)].

Infusion-Related Reactions

- Advise patients of the potential risk of infusion-related reactions [see Warnings and Precautions (5.2)].

Complications of Allogeneic HSCT

- Advise patients of potential risk of post-transplant complications [see Warnings and Precautions (5.3)].

Embryo-Fetal Toxicity

- Advise females of reproductive potential of the potential risk to a fetus and to inform their healthcare provider of a known or suspected pregnancy [see Warnings and Precautions (5.4), Use in Specific Populations (8.1)].
- Advise females of reproductive potential to use effective contraception during treatment with OPDUALAG and for at least 5 months following the last dose [see Use in Specific Populations (8.3)].

Lactation

- Advise women not to breastfeed during treatment with OPDUALAG and for 5 months after the last dose [see Use in Specific Populations (8.2)].

Manufactured by:

Bristol-Myers Squibb Company

Princeton, NJ 08543 USA

U.S. License No. 1713

Medication Guide

OPDUALAG™ (op-DEW-uh-lag)

(nivolumab and relatlimab-rmbw)

injection

What is the most important information I should know about OPDUALAG?

OPDUALAG is a medicine that may treat a type of skin cancer called melanoma by working with your immune system. OPDUALAG can cause your immune system to attack normal organs and tissues in any area of your body and can affect the way they work. These problems can sometimes become severe or can lead to death. These problems may happen anytime during treatment or even after your treatment has ended. You may have more than one of these problems at the same time.

Call or see your healthcare provider right away if you develop any new or worse signs of symptoms, including:

Lung problems.

- new or worsening cough

- shortness of breath

- chest pain

Intestinal problems.

- diarrhea (loose stools) or more frequent bowel movements than usual
- stool that are black, tarry, sticky, or have blood or mucus
- severe stomach-area (abdominal) pain or tenderness

Liver problems.

- yellowing of your skin or the whites of your eyes
- severe nausea or vomiting
- pain on the right side of your stomach area (abdomen)

- dark urine (tea colored)
- bleeding or bruising more easily than normal

Hormone gland problems.

- headaches that will not go away or unusual headaches
- eye sensitivity to light
- eye problems
- rapid heartbeat
- increased sweating
- extreme tiredness
- weight gain or weight loss
- feeling more hungry or thirsty than usual

- urinating more often than usual
- hair loss
- feeling cold
- constipation
- your voice gets deeper
- dizziness or fainting
- changes in mood or behavior, such as decreased sex drive, irritability, or forgetfulness

Kidney problems.

- decrease in your amount of urine
- blood in your urine

- swelling in your ankles
- loss of appetite

Skin problems.

- rash
- itching

- skin blistering or peeling
- painful sore or ulcers in mouth or nose, throat, or genital area

Heart problems.

- new or worse chest pain
- irregular heartbeat or feel like your heart is racing
- shortness of breath

- tiredness
- swelling in your ankles

Problems can also happen in other organs and tissues. These are not all of the signs and symptoms of immune system problems that can happen with OPDUALAG. Call or see your healthcare provider right away for any new or worsening sign or symptoms, which may include:

- Confusion, sleepiness, memory problems, changes in mood or behavior, stiff neck, balance problems, tingling or numbness of the arms or legs
- Double vision, blurry vision, sensitivity to light, eye pain, changes in eyesight
- Persistent or severe muscle pain or weakness, muscle cramps
- Low red blood cells, bruising

Getting medical treatment right away may keep these problems from becoming more serious.

Your healthcare provider will check you for these problems during treatment with OPDUALAG. Your healthcare provider may treat you with corticosteroid or hormone replacement medicines. Your healthcare provider may also need to delay or completely stop treatment with OPDUALAG, if you have severe side effects.

What is OPDUALAG?

OPDUALAG is a prescription medicine used to treat:

- adults and children 12 years of age or older with a type of skin cancer called melanoma that has spread or cannot be removed by surgery.

It is not known if OPDUALAG is safe and effective when used:

- in children 12 years of age or older who weigh less than 88 pounds (40 kg), or
- in children younger than 12 years of age.

Before you receive OPDUALAG, tell your healthcare provider if you:

- have immune system problems such as Crohn’s disease, ulcerative colitis, or lupus
- have received an organ transplant
- have received or plan to receive a stem cell transplant that uses donor stem cells (allogeneic)
- have a condition that affects your nervous system, such as myasthenia gravis or Guillain-Barré syndrome
- are pregnant or plan to become pregnant. OPDUALAG can harm your unborn baby.
Females who are able to become pregnant:
  1. Your healthcare provider should do a pregnancy test before you start receiving OPDUALAG.
  2. You should use an effective method of birth control during and for at least 5 months after the last dose of OPDUALAG. Talk to your healthcare provider about birth control methods that you can use during this time.
  3. Tell your healthcare provider right away if you become pregnant during treatment with OPDUALAG.
- are breastfeeding or plan to breastfeed. It is not known if OPDUALAG passes into your breast milk. Do not breastfeed during treatment with OPDUALAG and for 5 months after the last dose of OPDUALAG.

Tell your healthcare provider about all the medicines you take, including prescription and over-the-counter medicines, vitamins, and herbal supplements.

How will I receive OPDUALAG?

- Your healthcare provider will give you OPDUALAG into your vein through an intravenous (IV) line over 30 minutes.
- OPDUALAG is usually given every 4 weeks.
- Your healthcare provider will decide how many treatments you need.
- Your healthcare provider will do blood tests to check you for side effects.
- If you miss any appointments, call your healthcare provider as soon as possible to reschedule your appointment.

What are the possible side effects of OPDUALAG?

OPDUALAG can cause serious side effects, including:

- See “What is the most important information I should know about OPDUALAG?”
- Severe infusion reactions. Tell your healthcare provider or nurse right away if you get these symptoms during an infusion of OPDUALAG:

- chills or shaking
- itching or rash
- flushing
- shortness of breath

- dizziness
- feel like passing out
- fever
- back or neck pain

- Complications of stem cell transplant that uses donor stem cells (allogeneic). These complications can be severe and can lead to death. These complications may happen if you underwent transplantation either before or after being treated with OPDUALAG. Your healthcare provider will monitor you for signs of complications if you have an allogeneic stem cell transplant.

The most common side effects of OPDUALAG include:

- muscle and bone pain
- tiredness
- decreased red blood cell and white blood cell counts
- increased liver function test results

- rash
- itching
- diarrhea
- decreased salt (sodium) in your blood

These are not all the possible side effects of OPDUALAG.

Call your doctor for medical advice about side effects. You may report side effects to FDA at 1-800-FDA-1088.

General information about the safe and effective use of OPDUALAG.

Medicines are sometimes prescribed for purposes other than those listed in a Medication Guide. You can ask your pharmacist or healthcare provider for information about OPDUALAG that is written for health professionals.

What are the ingredients in OPDUALAG?

Active ingredients: nivolumab and relatlimab

Inactive ingredients: histidine, L-histidine hydrochloride monohydrate, pentetic acid, polysorbate 80, sucrose, and Water for Injection.

OPDUALAG™ is trademark of Bristol-Myers Squibb Company. Other brands listed are the trademarks of their respective owners.

Manufactured by: Bristol-Myers Squibb Company Princeton, NJ 08543 USA U.S. License No. 1713

For more information, call 1-855-673-4861 or go to www.OPDUALAG.com.

This Medication Guide has been approved by the U.S. Food and Drug Administration. Revised: March 2022

OPDUALAG 240 mg and 80 mg/20 mL Representative Packaging

NDC 0003-7125-11

Rx only

OpdualagTM

(nivolumab and relatlimab -rmbw)

Injection

240 mg and 80 mg/20 mL

(12 mg and 4 mg/mL)

For Intravenous Infusion Only

Single-dose vial; Discard unused portion.

Please provide enclosed Medication Guide to the patient.

Bristol Myers Squibb